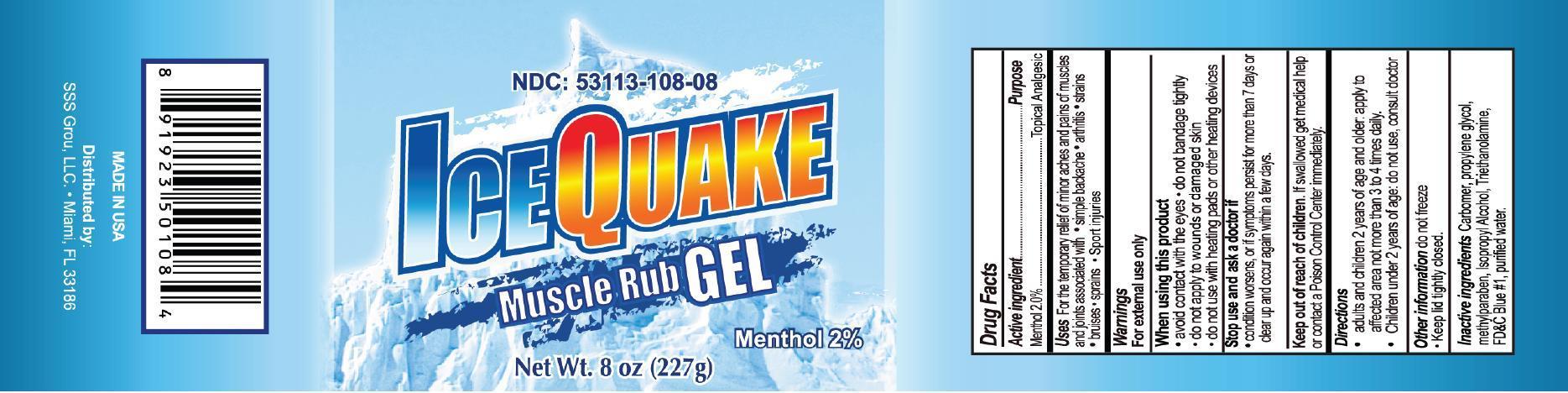 DRUG LABEL: Ice Quake
NDC: 53113-108 | Form: GEL
Manufacturer: Gadal Laboratories Inc
Category: otc | Type: HUMAN OTC DRUG LABEL
Date: 20130916

ACTIVE INGREDIENTS: MENTHOL 2 g/100 g
INACTIVE INGREDIENTS: CARBOMER 940; PROPYLENE GLYCOL; METHYLPARABEN; ISOPROPYL ALCOHOL; TROLAMINE; FD&C BLUE NO. 1; Water

Active Ingredients Purpose

Menthol 2.0% Topical Anagesic

Purpose

Topical Analgesic

Uses

For the temporary relief of minor aches and pains of muscles and joints associated with

- simple backache
- arthritis
- strains
- bruises
- sprains
- sport injuries

Warnings

For external use only

When using this product

- avoid contact with the eyes
- do not bandage tightly
- do not apply to wounds or damaged skin
- do not use with heating pads or ther heating devices

Stop use and ask a doctor if

condition worsens, or if symptoms persist for more than 7 days or clear up and occur again within a few days

Keep out of reach of children. If swallowed get medical help or contact a Poison Control Center immediately.

Directions

- adults and children 2 years of age and older; apply to affected area not more than 3 to 4 times daily.
- children under 2 years of age; do not use, consult doctor

INACTIVE INGREDIENT

Inactive ingredients carbomer, propylene glycol, methylparaben, isopropyl alcohol, triethanolamine, FD&C Blue #1, water

QUESTIONS

SSS Grou, LLC Miami, Fl 33183